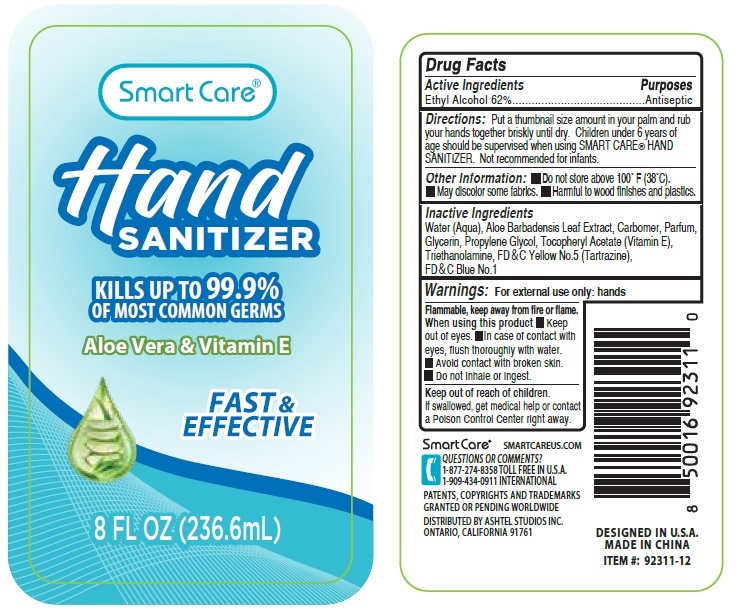 DRUG LABEL: Smart Care Hand Sanitizer 8 oz
NDC: 72285-002 | Form: GEL
Manufacturer: Yozzi Co.,ltd
Category: otc | Type: HUMAN OTC DRUG LABEL
Date: 20200423

ACTIVE INGREDIENTS: ALCOHOL 62 mL/100 mL
INACTIVE INGREDIENTS: WATER; ALOE VERA LEAF; CARBOMER HOMOPOLYMER, UNSPECIFIED TYPE; GLYCERIN; PROPYLENE GLYCOL; .ALPHA.-TOCOPHEROL ACETATE; TROLAMINE; FD&C YELLOW NO. 5; FD&C BLUE NO. 1

Smart Care® Hand SANITIZER

Active Ingredients

Ethyl Alcohol 62%

Purposes

Antiseptic

Uses

For external use only: hands

Directions

Put a thumbnail size amount in your palm and rub your hands together briskly until dry. Children under 6 years of age should be supervised when using SMART CARE® HAND SANITIZER. Not recommended for infants.

Other Information

▪ Do not store above 100°F (38°C).
▪ May discolor some fabrics.
▪ Harmful to wood finishes and plastics.

Inactive Ingredients

Water (Aqua), Aloe Barbadensis Leaf Extract, Carbomer, Parfum, Glycerin, Propylene Glycol, Tocopheryl Acetate (Vitamin E), Triethanolamine, FD&C Yellow No. 5(Tartrazine), FD&C Blue No. 1

Warnings:

For external use only: hands

Flammable. Keep away from fire or flame.

When using this product

▪ Keep out of eyes.

▪ In case of contact with eyes, flush thoroughly with water.

▪ Avoid contact with broken skin.

▪ Do not inhale or ingest.

Keep out of reach of children.

If swallowed, get medical help or contact a Poison Control Center right away.

KILLS UP TO 99.9% OF MOST COMMON GERMS

Aloe Vera & Vitamin E

FAST & EFFECTIVE

SMARTCAREUS.COM

QUESTIONS OR COMMENTS?

1-877-274-8358 TOLL FREE IN U.S.A.

1-909-434-0911 INTERNATIONAL

PATENTS, COPYRIGHTS AND TRADEMARKS GRANTED OR PENDING WORLDWIDE

DISTRIBUTED BY ASHTEL STUDIOS INC. ONTARIO, CALIFORNIA 91761

DESIGNED IN U.S.A. • MADE IN CHINA